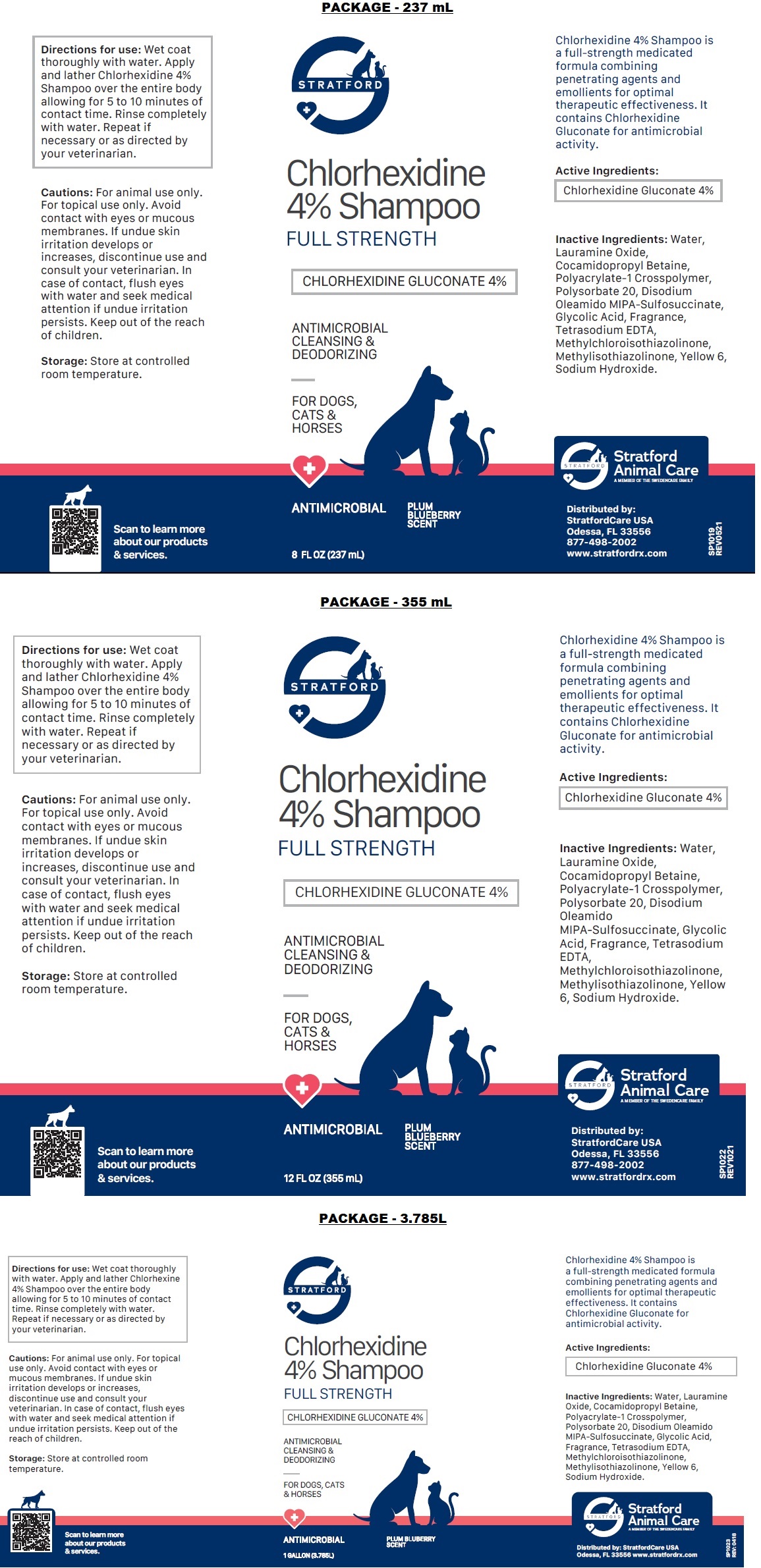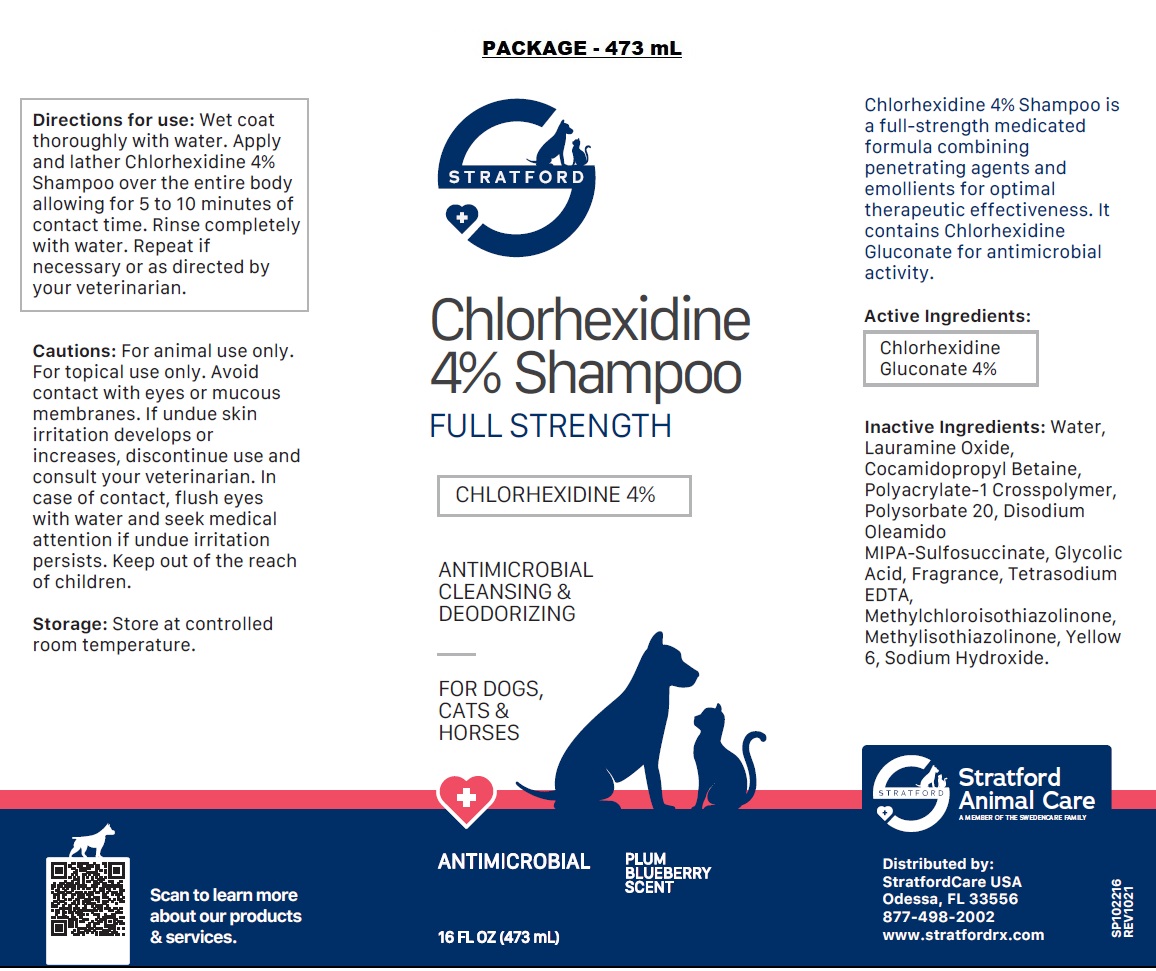 DRUG LABEL: Chlorhexidine 4%
NDC: 86069-104 | Form: SHAMPOO
Manufacturer: Stratford Care Usa, Inc.
Category: animal | Type: OTC ANIMAL DRUG LABEL
Date: 20221219

ACTIVE INGREDIENTS: CHLORHEXIDINE GLUCONATE 4 g/100 mL
INACTIVE INGREDIENTS: WATER; LAURAMINE OXIDE; COCAMIDOPROPYL BETAINE; POLYACRYLATE-1 CROSSPOLYMER; POLYSORBATE 20; DISODIUM OLEAMIDO MIPA-SULFOSUCCINATE; GLYCOLIC ACID; EDETATE SODIUM; METHYLCHLOROISOTHIAZOLINONE; METHYLISOTHIAZOLINONE; FD&C YELLOW NO. 6; SODIUM HYDROXIDE

Chlorhexidine 4% SHAMPOO

Active Ingredients:

Chlorhexidine Gluconate 4%

PURPOSE

ANTIMICROBIAL

INDICATIONS AND USAGE

Chlorhexidine 4% Shampoo is a full-strength medicated formula combining penetrating agents and emollients for optimal therapeutic effectiveness. It contains Chlorhexidine Gluconate for antimicrobial activity.

INACTIVE INGREDIENT

Inactive Ingredients: Water, Lauramine Oxide, Cocamidopropyl Betaine, Polyacrylate-1 Crosspolymer, Polysorbate 20, Disodium Oleamido MIPA-Sulfosuccinate, Glycolic Acid, Fragrance, Tetrasodium EDTA, Methylchloroisothiazolinone, Methylisothiazolinone, Yellow 6, Sodium Hydroxide.

DOSAGE AND ADMINISTRATION

Directions for use: Wet coat thoroughly with water. Apply and lather Chlorhexidine 4% Shampoo over the entire body allowing for 5 to 10 minutes of contact time. Rinse completely with water. Repeat if necessary or as directed by your veterinarian.

PRECAUTIONS

Cautions: For animal use only. For topical use only. Avoid contact with eyes or mucous membranes. If undue skin irritation develops or increases, discontinue use and consult your veterinarian. In case of contact, flush eyes with water and seek medical attention if undue irritation persists. Keep out of the reach of children.

Storage: Store at controlled room temperature.

FULL STRENGTH

ANTIMICROBIAL CLEANSING & DEODORIZING

FOR DOGS, CATS & HORSES

PLUM BLUEBERRY SCENT

Stratford Animal Care
A MEMBER OF THE SWEDENCARE FAMILY

Distributed by:
StratfordCare USA
Odessa, FL 33556
877-498-2002
www.stratfordrx.com